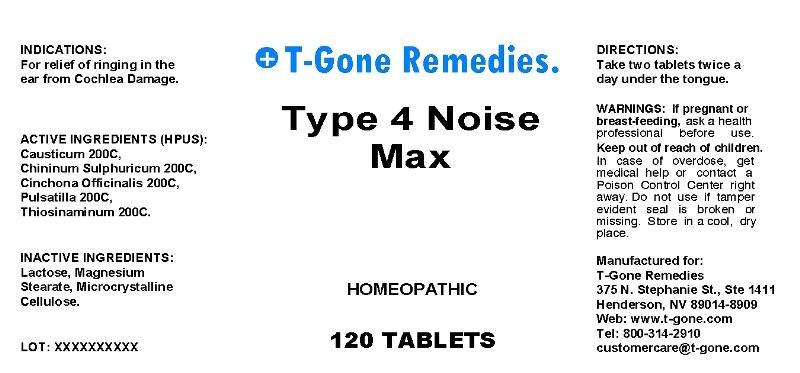 DRUG LABEL: Type 4 Noise Max
NDC: 50169-0003 | Form: TABLET, ORALLY DISINTEGRATING
Manufacturer: T Gone Remedies
Category: homeopathic | Type: HUMAN OTC DRUG LABEL
Date: 20130410

ACTIVE INGREDIENTS: CAUSTICUM 200 [hp_C]/1 mg; QUININE SULFATE 200 [hp_C]/1 mg; CINCHONA OFFICINALIS BARK 200 [hp_C]/1 mg; PULSATILLA VULGARIS 200 [hp_C]/1 mg; ALLYLTHIOUREA 200 [hp_X]/1 mg
INACTIVE INGREDIENTS: LACTOSE; MAGNESIUM STEARATE; CELLULOSE, MICROCRYSTALLINE

Drug Facts

ACTIVE INGREDIENTS

Causticum 200C, Chininum Sulphuricum 200C, Cinchona Officinalis 200C, Pulsatilla 200C, Thiosinaminum 200C

INDICATIONS

For relief of ringing in the ear from Cochlea Damage.

WARNINGS

If pregnant or breast-feeding, ask a health professional before use. Keep out of reach of children. In case of overdose, get medical help or contact a Poison Control Center right away. Do not use if tamper evident seal is broken or missing. Store in a cool, dry place.

DIRECTIONS

Take two tablets twice a day under the tongue.

INACTIVE INGREDIENTS

Lactose, Magnesium Stearate, Microcrystalline Cellulose

KEEP OUT OF REACH OF CHILDREN

In case of overdose, get medical help or contact a Poison Control Center right away.

INDICATIONS AND USAGE

For relief of ringing in the ear from Cochlea Damage.

QUESTIONS

Manufactured for:

T Gone Remedies

375 N. Stephanie St., 1411

Henderson, NV 89014-8909

Web: www.t-gone.com

Tel: 800-314-2910

PACKAGE LABEL

T Gone Remedies

Type 4 Noise

Max

HOMEOPATHIC

120 Tablets